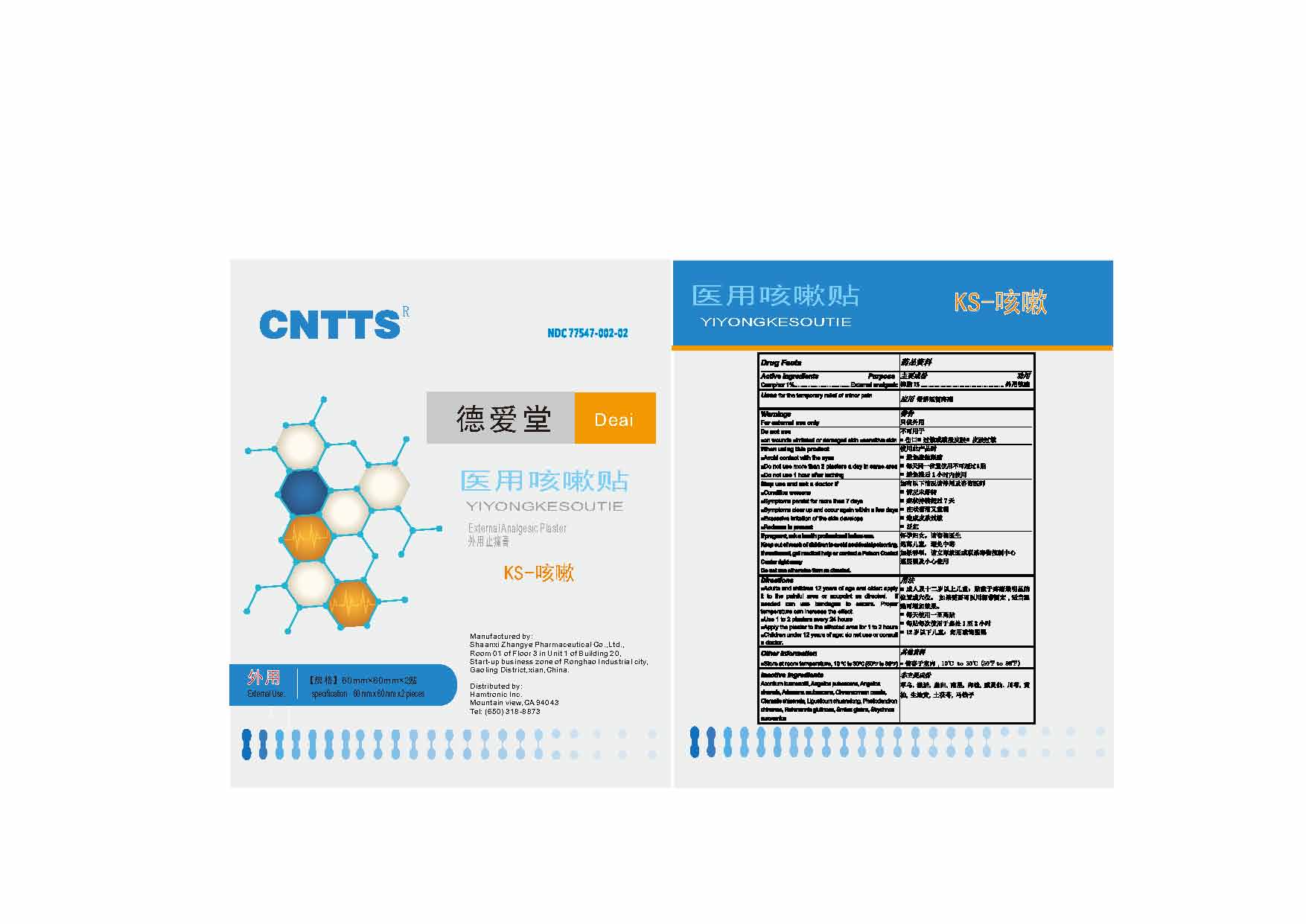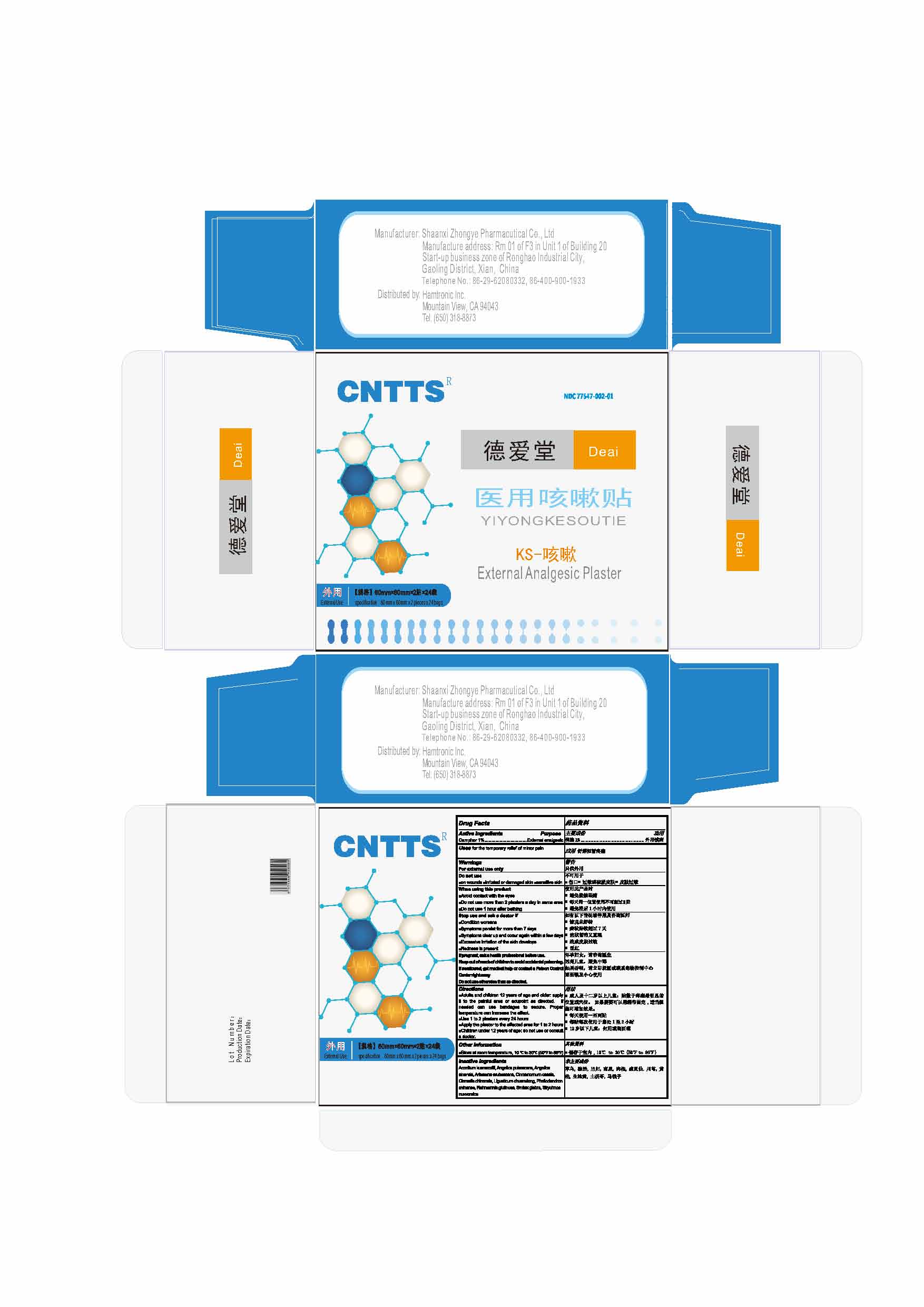 DRUG LABEL: Yiyongkesoutie
NDC: 77547-002 | Form: PLASTER
Manufacturer: Beijing Shenzhou Pharmaceutical Technology Co., Ltd
Category: otc | Type: HUMAN OTC DRUG LABEL
Date: 20200619

ACTIVE INGREDIENTS: CAMPHOR (NATURAL) 1 g/100 g
INACTIVE INGREDIENTS: ACONITUM KUSNEZOFFII WHOLE; ANGELICA PUBESCENS WHOLE; ANGELICA SINENSIS ROOT; ARISAEMA ERUBESCENS WHOLE; CINNAMOMUM CASSIA TWIG; CLEMATIS CHINENSIS ROOT; LIGUSTICUM SINENSE SUBSP. CHUANXIONG ROOT; PHELLODENDRON CHINENSIS BARK; REHMANNIA GLUTINOSA WHOLE; SMILAX GLABRA TUBER; STRYCHNOS NUX-VOMICA SEED

Yiyongxueweitie

Active ingredients

Camphor 1%.................……….…….External analgesic

Do not use otherwise than as directed

Keep out of reach of children to avoid accidental poisoning

If swallowed, get medical help or contact a Poison Control Center right away

If pregnant

If pregnant, ask a health professional before use

Directions

■Adults and children 12 years of age and older: apply it to the painful area or acupoint as directed. If needed can use bandages to secure. Proper temperature can increase the effect.
■Use 1 to 2 plasters every 24 hours
■Apply the plaster to the affected area for 1 to 2 hours
■Children under 12 years of age: do not use or consult a doctor.

Other information

■Store at room temperature, 10 ℃ to 30℃ (50℉ to 86℉)

Inactive ingredients

Achyranthes bidentate, Aconitum carmichaeli, Angelica sinensis, Arisaema erubescens, Carthamus tinctorius, Cinnamomum cassia, Ligusticum chuanxiong, Notopterygium incisum, Paeonia lactiflora, Speranskia tuberculate, Zingiber officinale

Purpose

External analgesic

Do not use

■on wounds

■irritated or damaged skin

■sensitive skin

When using this product

■Avoid contact with the eyes
■Do not use more than 2 plasters a day in same area
■Do not use 1 hour after bathing

Stop use and ask a doctor if

■Condition worsens
■Symptoms persist for more than 7 days
■Symptoms clear up and occur again within a few days
■Excessive irritation of the skin develops
■Redness is present

Use

For external use only

Uses

Uses for the temporary relief of minor pain

Inner Bag

External Box